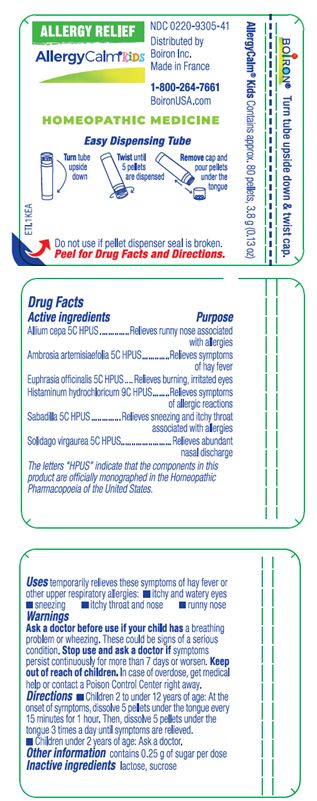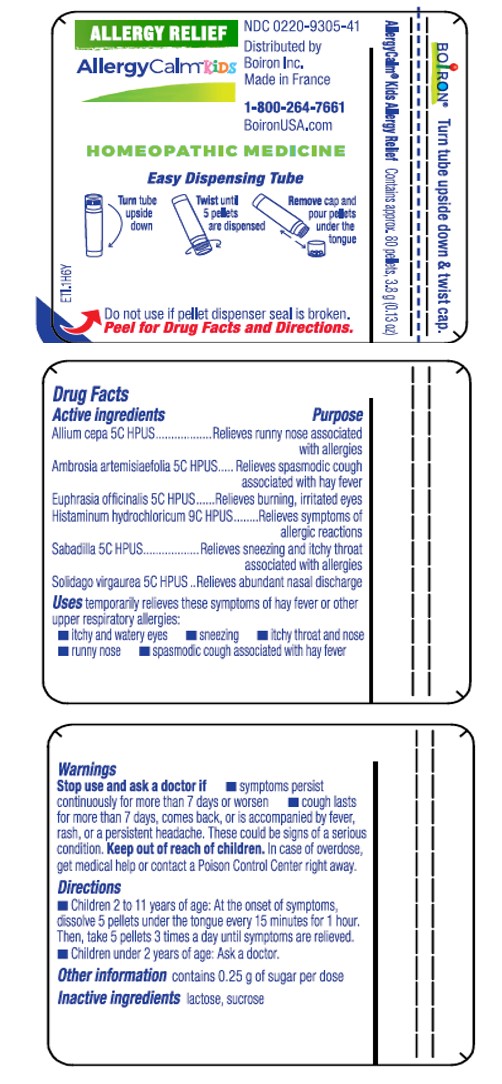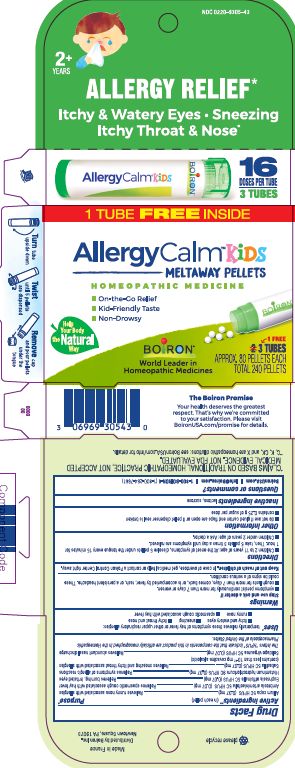 DRUG LABEL: ALLERGYCALM
NDC: 0220-9305 | Form: PELLET
Manufacturer: Boiron
Category: homeopathic | Type: HUMAN OTC DRUG LABEL
Date: 20250925

ACTIVE INGREDIENTS: HISTAMINE DIHYDROCHLORIDE 9 [hp_C]/1 1; SOLIDAGO VIRGAUREA FLOWERING TOP 5 [hp_C]/1 1; ONION 5 [hp_C]/1 1; AMBROSIA ARTEMISIIFOLIA 5 [hp_C]/1 1; SCHOENOCAULON OFFICINALE SEED 5 [hp_C]/1 1; EUPHRASIA STRICTA 5 [hp_C]/1 1
INACTIVE INGREDIENTS: LACTOSE, UNSPECIFIED FORM; SUCROSE

AllergyCalm Kids Pellets

Active ingredients** (in each pellet)

Allium cepa 5C HPUS (0.07 mg)

Ambrosia artemisiaefolia 5C HPUS (0.07 mg)

Euphrasia officinalis 5C HPUS (0.07 mg)

Histaminum hydrochloricum 9C HPUS (0.07 mg)

Sabadilla 5C HPUS (0.07 mg) (contains less than 10^-12 mg cevadine alkaloids)

Solidago virgaurea 5C HPUS (0.07 mg)

The letters "HPUS" indicate that the components in this product are officially monographed in the Homeopathic Pharmacopoeia of the United States.

Purpose*

Allium cepa 5C HPUS (0.07 mg) ... Relieves runny nose associated with allergies

Ambrosia artemisiaefolia 5C HPUS (0.07 mg) ... Relieves symptoms of hay fever

Euphrasia officinalis 5C HPUS (0.07 mg) ... Relieves burning, irritated eyes

Histaminum hydrochloricum 9C HPUS (0.07 mg) ... Relieves symptoms of allergic reactions

Sabadilla 5C HPUS (0.07 mg) ... Relieves sneezing and itchy throat associated with allergies

Solidago virgaurea 5C HPUS (0.07 mg) ... Relieves abundant nasal discharge

Uses*

temporarily relieves these symptoms of hay fever or other upper respiratory allergies:

- itchy and watery eyes
- sneezing
- itchy throat and nose
- runny nose

Ask a doctor before use if your child has a breathing problem or wheezing. These could be signs of a serious condition.

Stop use and ask a doctor if symptoms persist continuously for more than 7 days or worsen.

Keep out of reach of children. In case of overdose, get medical help or contact a Poison Control Center right away.

Directions

- Children 2 to under 12 years of age: At the onset of symptoms, dissolve 5 pellets under the tongue every 15 minutes for 1 hour. Then, dissolve 5 pellets under the tongue 3 times a day until symptoms are relieved.
- Children under 2 years of age: Ask a doctor.

Other information

- do not use if glued carton end flaps are open or if pellet dispenser seal is broken
- contains 0.25 g of sugar per dose

INACTIVE INGREDIENT

lactose, sucrose

Questions or comments?

BoironUSA.com

Info@Boiron.com

1-800-BOIRON-1 (1-800-264-7661)

3 TUBES

APPROX. 80 PELLETS EACH

TOTAL 240 PELLETS

16 DOSES PER TUBE

Allergy Relief*

Itchy & Watery Eyes, Sneezing, Itchy Throat & Nose*

Turn tube upside down

Twist until 5 pellets are dispensed

Remove cap and pour pellets under the tongue

*CLAIMS BASED ON TRADITIONAL HOMEOPATHIC PRACTICE, NOT ACCEPTED MEDICAL EVIDENCE. NOT FDA EVALUATED.
*C,K,CK, and X are homeopathic dilutions: see BoironUSA.com/info for details.